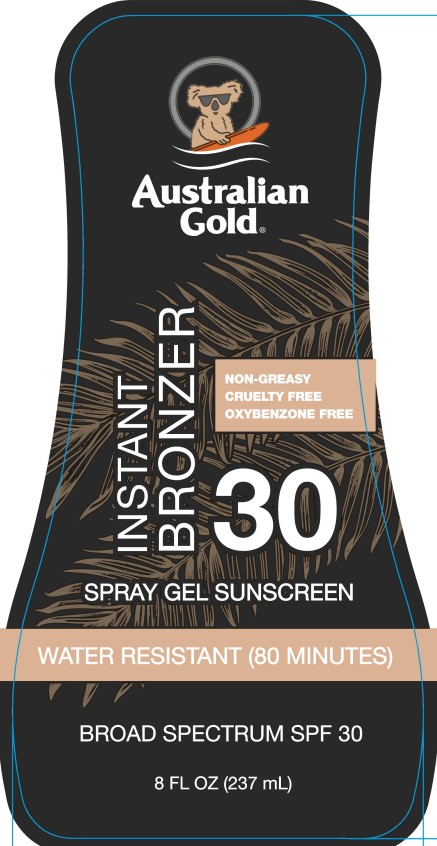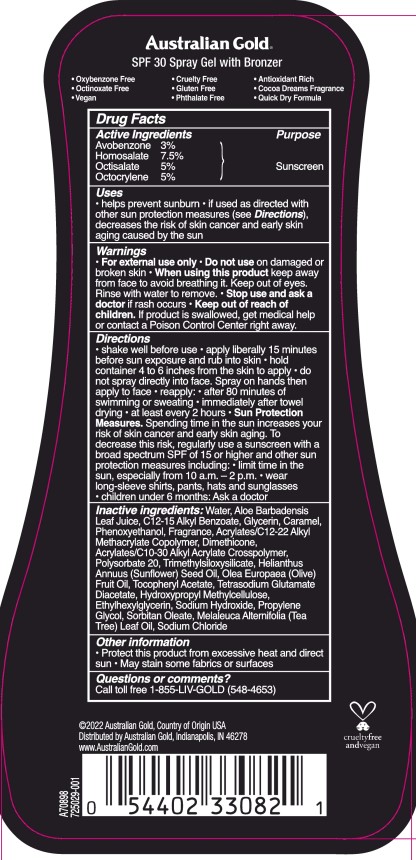 DRUG LABEL: Austalian Gold
NDC: 58443-0589 | Form: SPRAY
Manufacturer: Prime Enterprises Inc.
Category: otc | Type: HUMAN OTC DRUG LABEL
Date: 20221116

ACTIVE INGREDIENTS: OCTOCRYLENE 50.1 g/1 mL; AVOBENZONE 30.06 g/1 mL; OCTISALATE 50.1 g/1 mL; HOMOSALATE 75.15 g/1 mL
INACTIVE INGREDIENTS: PROPYLENE GLYCOL; FRAGRANCE LAVENDER & CHIA F-153480; GLYCERIN; TRIMETHYLSILOXYSILICATE (M/Q 0.6-0.8); SUNFLOWER OIL; ETHYLHEXYLGLYCERIN; TETRASODIUM GLUTAMATE DIACETATE; HYPROMELLOSES; OLIVE OIL; SODIUM HYDROXIDE; SORBITAN MONOOLEATE; KAKADU PLUM; PHENOXYETHANOL; POLYSORBATE 20; ALPHA-TOCOPHEROL ACETATE; WATER; ALOE VERA LEAF; CARAMEL; DIMETHICONE; CARBOMER COPOLYMER TYPE B (ALLYL PENTAERYTHRITOL CROSSLINKED); BUTYL ACRYLATE/METHYL METHACRYLATE/METHACRYLIC ACID COPOLYMER (18000 MW); ALKYL (C12-15) BENZOATE; TEA TREE OIL

Australian Gold Instant Bronzer Spray Gel Broad Spectrum SPF 30

Active Ingredients

Avobenzone 3.0%

Homosalate 7.5%

Octisalate 5.0%

Octocrylene 5.0%

Purpose

Sunscreen

Uses

- helps prevent sunburn
  - if used as directed with other sun protection measures (see Directions) decreases the risk of skin cancer and early skin aging caused by the sun

Warnings

For external use only

Do not use on damaged or broken skin

When using this product keep out of eyes. Rinse with water to remove.

Stop use and ask a doctor if rash occurs

Keep out of reach of children. If product is swallowed, get medical help or contact a Poison Control Center right away.

Directions

- shake well before use
- apply liberally 15 minutes before sun exposure and rub into skin
- hold container 4 to 6 inches from the skin to apply
- do not spray directly into face
- spray on hands then apply to face
- reapply:
- after 80 minutes of swimming or sweating
- immediately after towel drying
- at least every 2 hours
- Sun Protection Measures Spending time ine the sun increases your risk of skin cancer and early skin aging. To decrease this risk, regularly use a sunscreen with a broad spectrum SPF valvue of 15 or higher and other sun protecion measures including:
- limit tim ein the sun, especially from 10am-2pm
- wear long sleeve shirts, pants, hats, and sunglasses
- children under 6 months: Ask a doctor

Inactive Ingredients

Water, Aloe Barbadensis Leaf Juice, C12-15 Alkyl Benzoate, Glycerin, Phenoxyethanol, Caramel, Phenoxyethanol, Fragrance, Acrylates/C12-22 Alkyl Methacrylate Copolymer, Dimethicone, Acrylates/C10-30 Alkyl Acrylate Crosspolymer, Polysorbate 20, Trimethylsiloxysilicate, Helianthus Annuus (Sunflower) Seed Oil, Olea Europaea (Olive) Fruit Oil, Tocopheryl Acetate, Tetrasodium Glutamate Diacetate, Hydroxypropyl Methylcellulose, Ethylhexylglycerin, Sodium Hydroxide, Propylene Glycol, Sorbitan Oleate, Melaleuca Alternifolia (Tea Tree) Leaf Oil, Sodium Chloride

Other Information

- Protect this product from excesive heat and direct sun
- May stain some frabics or surfaces

Questions or Comments?

Call Toll free 1-855-LIV-GOLD (548-4653)